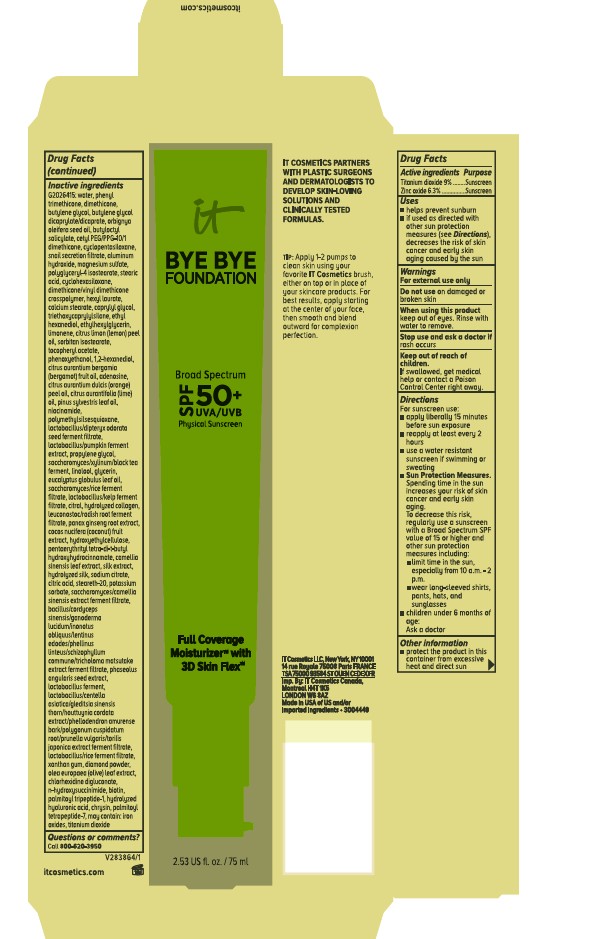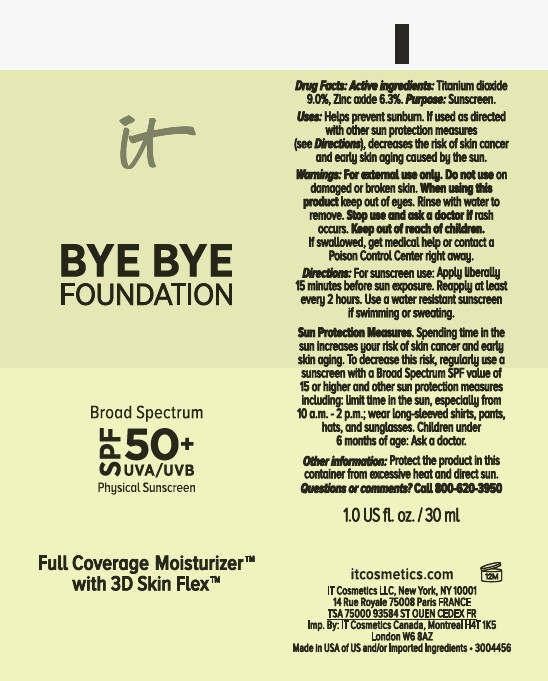 DRUG LABEL: it cosmetics Bye Bye Foundation Full Coverage Moisturizer with 3D Skin Flex Broad Spectrum SPF 50 Plus UVA UVB Physical Sunscreen All Shades
NDC: 82046-334 | Form: LOTION
Manufacturer: L'Oreal USA, Inc.
Category: otc | Type: HUMAN OTC DRUG LABEL
Date: 20251124

ACTIVE INGREDIENTS: TITANIUM DIOXIDE 90 mg/1 mL; ZINC OXIDE 63 mg/1 mL
INACTIVE INGREDIENTS: WATER; PHENYL TRIMETHICONE; DIMETHICONE; BUTYLENE GLYCOL; BUTYLENE GLYCOL DICAPRYLATE/DICAPRATE; BABASSU OIL; BUTYLOCTYL SALICYLATE; CETYL PEG/PPG-10/1 DIMETHICONE (HLB 2); CYCLOMETHICONE 5; SNAIL SECRETION FILTRATE; ALUMINUM HYDROXIDE; MAGNESIUM SULFATE, UNSPECIFIED FORM; POLYGLYCERYL-4 ISOSTEARATE; STEARIC ACID; CYCLOMETHICONE 6; DIMETHICONE/VINYL DIMETHICONE CROSSPOLYMER (HARD PARTICLE); HEXYL LAURATE; CALCIUM STEARATE; CAPRYLYL GLYCOL; TRIETHOXYCAPRYLYLSILANE; ETHOHEXADIOL; ETHYLHEXYLGLYCERIN; LIMONENE, (+)-; LEMON OIL; SORBITAN ISOSTEARATE; .ALPHA.-TOCOPHEROL ACETATE; PHENOXYETHANOL; 1,2-HEXANEDIOL; BERGAMOT OIL; ADENOSINE; ORANGE OIL; LIME OIL; PINE NEEDLE OIL (PINUS SYLVESTRIS); NIACINAMIDE; POLYMETHYLSILSESQUIOXANE (4.5 MICRONS); PROPYLENE GLYCOL; LINALOOL, (+/-)-; glycerin; EUCALYPTUS GLOBULUS LEAF OIL; CITRAL; LEUCONOSTOC/RADISH ROOT FERMENT FILTRATE; ASIAN GINSENG; COCOS NUCIFERA (COCONUT) FRUIT; HYDROXYETHYLCELLULOSE; PENTAERYTHRITYL TETRA-DI-T-BUTYL HYDROXYHYDROCINNAMATE; CAMELLIA SINENSIS LEAF; SILK, BASE HYDROLYZED (1000 MW); SODIUM CITRATE; CITRIC ACID; STEARETH-20; POTASSIUM SORBATE; ADZUKI BEAN; LIMOSILACTOBACILLUS FERMENTUM; XANTHAN GUM; DIAMOND POWDER; OLEA EUROPAEA (OLIVE) LEAF; CHLORHEXIDINE DIGLUCONATE; N-HYDROXYSUCCINIMIDE; BIOTIN; PALMITOYL TRIPEPTIDE-1; Chrysin; PALMITOYL TETRAPEPTIDE-7; FERRIC OXIDE RED; FERRIC OXIDE YELLOW; FERROSOFERRIC OXIDE

Drug Facts

Active ingredients

Titanium dioxide 9%

Zinc oxide 6.3%

Purpose

Sunscreen

Uses

- helps prevent sunburn

- if used as directed with other sun protection measures (see Directions), decreases the risk of skin cancer and early skin aging caused by the sun

Warnings

For external use only

Do not use

on damaged or broken skin

When using this product

keep out of eyes. Rinse with water to remove.

Stop use and ask a doctor if

rash occurs

Keep out of reach of children.

If swallowed, get medical help or contact a Poison Control Center right away.

Directions

For sunscreen use:

● apply liberally 15 minutes before sun exposure

● reapply at least every 2 hours

● use a water resistant sunscreen if swimming or sweating

● Sun Protection Measures. Spending time in the sun increases your risk of skin cancer and early skin aging. To decrease this risk,

regularly use a sunscreen with a Broad Spectrum SPF value of 15 or higher and other sun protection measures including:

● limit time in the sun, especially from 10 a.m. – 2 p.m.

● wear long-sleeved shirts, pants, hats, and sunglasses

● children under 6 months of age: Ask a doctor

Other information

protect the product in this container from excessive heat and direct sun

Inactive ingredients

G2026415: water, phenyl trimethicone, dimethicone, butylene glycol, butylene glycol dicaprylate/dicaprate, orbignya oleifera seed oil, butyloctyl salicylate, cetyl PEG/PPG-10/1 dimethicone, cyclopentasiloxane, snail secretion filtrate, aluminum hydroxide, magnesium sulfate, polyglyceryl-4 isostearate, stearic acid, cyclohexasiloxane, dimethicone/vinyl dimethicone crosspolymer, hexyl laurate, calcium stearate, caprylyl glycol, triethoxycaprylylsilane, ethyl hexanediol, ethylhexylglycerin, limonene, citrus limon (lemon) peel oil, sorbitan isostearate, tocopheryl acetate, phenoxyethanol, 1,2-hexanediol, citrus aurantium bergamia (bergamot) fruit oil, adenosine, citrus aurantium dulcis (orange) peel oil, citrus aurantifolia (lime) oil, pinus sylvestris leaf oil, niacinamide, polymethylsilsesquioxane, lactobacillus/dipteryx odorata seed ferment filtrate, lactobacillus/pumpkin ferment extract, propylene glycol, saccharomyces/xylinum/black tea ferment, linalool, glycerin, eucalyptus globulus leaf oil, saccharomyces/rice ferment filtrate, lactobacillus/kelp ferment filtrate, citral, hydrolyzed collagen, leuconostoc/radish root ferment filtrate, panax ginseng root extract, cocos nucifera (coconut) fruit extract, hydroxyethylcellulose, pentaerythrityl tetra-di-t-butyl hydroxyhydrocinnamate, camellia sinensis leaf extract, silk extract, hydrolyzed silk, sodium citrate, citric acid, steareth-20, potassium sorbate, saccharomyces/camellia sinensis extract ferment filtrate, bacillus/cordyceps sinensis/ganoderma lucidum/inonotus obliquus/lentinus edodes/phellinus linteus/schizophyllum commune/tricholoma matsutake extract ferment filtrate, phaseolus angularis seed extract, lactobacillus ferment, lactobacillus/centella asiatica/gleditsia sinensis thorn/houttuynia cordata extract/phellodendron amurense bark/polygonum cuspidatum root/prunella vulgaris/torilis japonica extract ferment filtrate, lactobacillus/rice ferment filtrate, xanthan gum, diamond powder, olea europaea (olive) leaf extract, chlorhexidine digluconate, n-hydroxysuccinimide, biotin, palmitoyl tripeptide-1, hydrolyzed hyaluronic acid, chrysin, palmitoyl tetrapeptide-7. May contain: iron oxides, titanium dioxide.

Questions or comments?

Call 800-620-3950